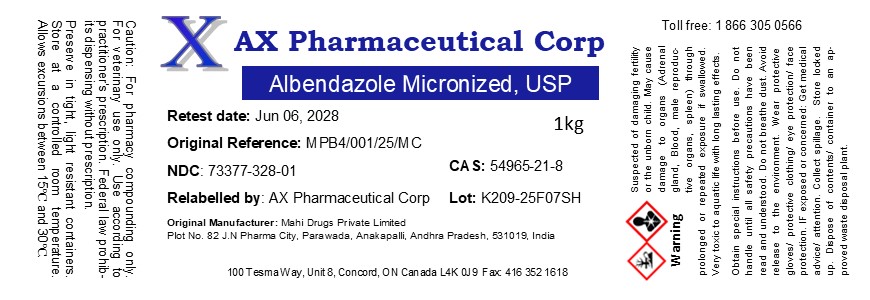 DRUG LABEL: Albendazole Micronized
NDC: 73377-328 | Form: POWDER
Manufacturer: AX Pharmaceutical Corp
Category: other | Type: BULK INGREDIENT - ANIMAL DRUG
Date: 20251124

ACTIVE INGREDIENTS: ALBENDAZOLE 1 g/1 g

Albendazole Micronized